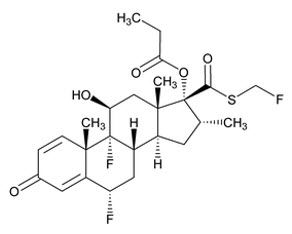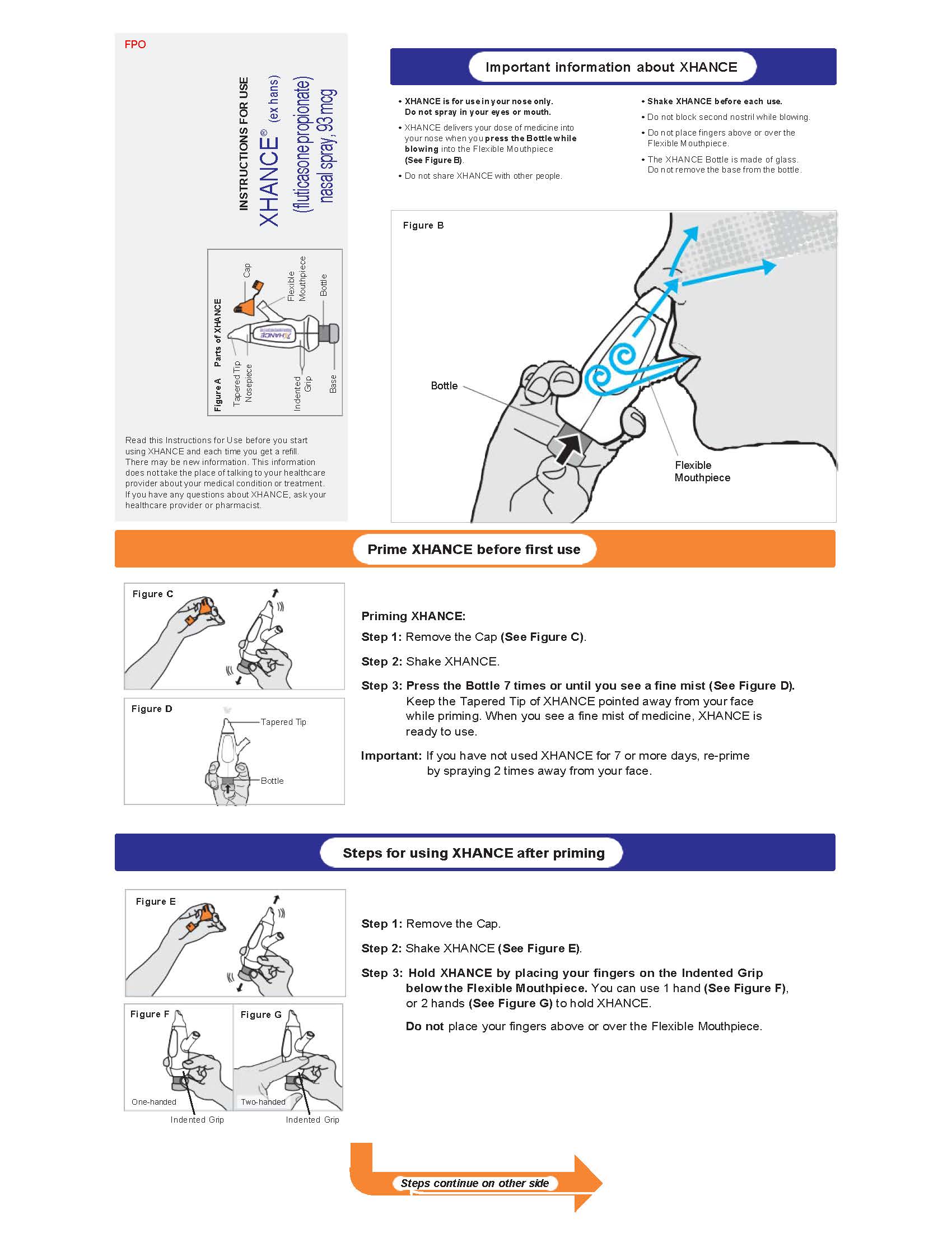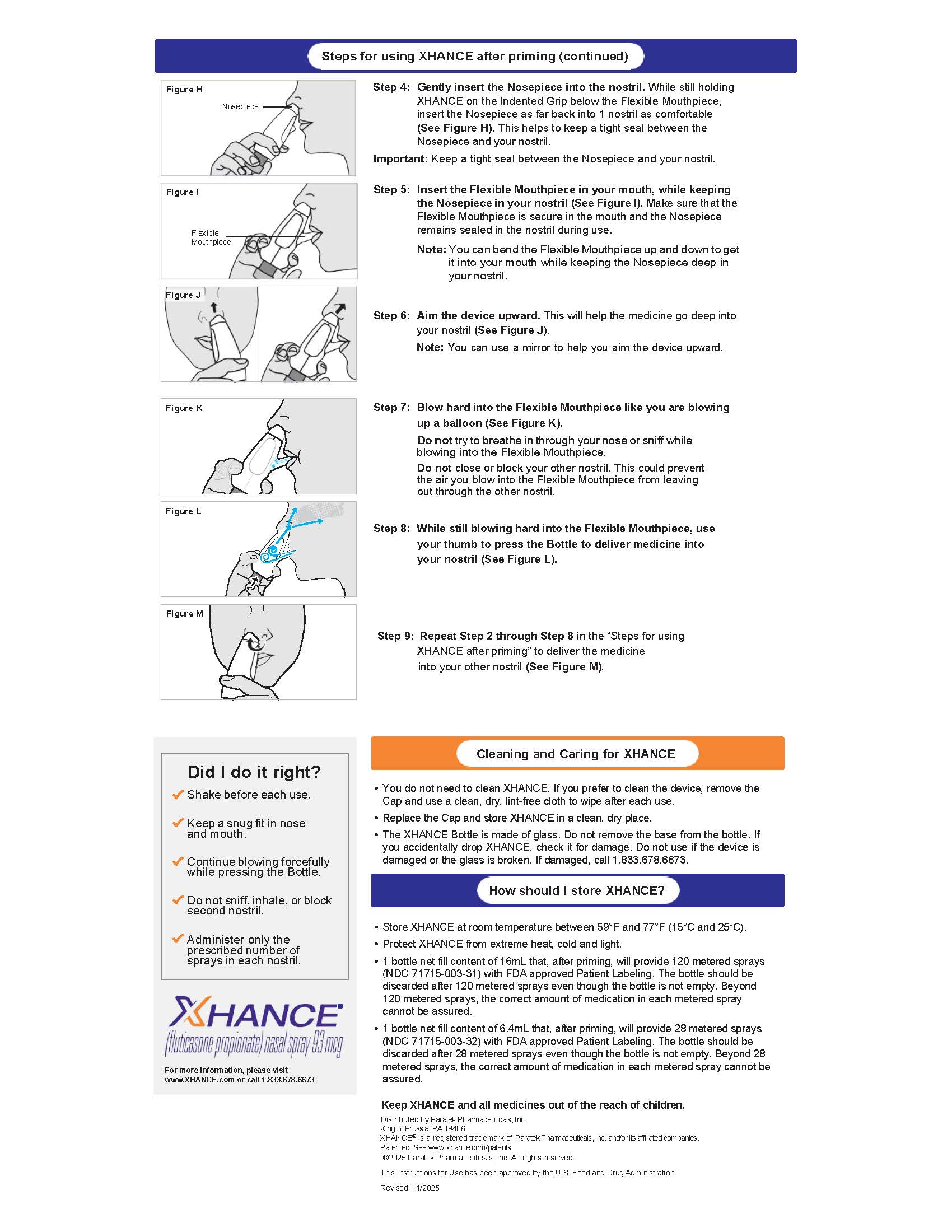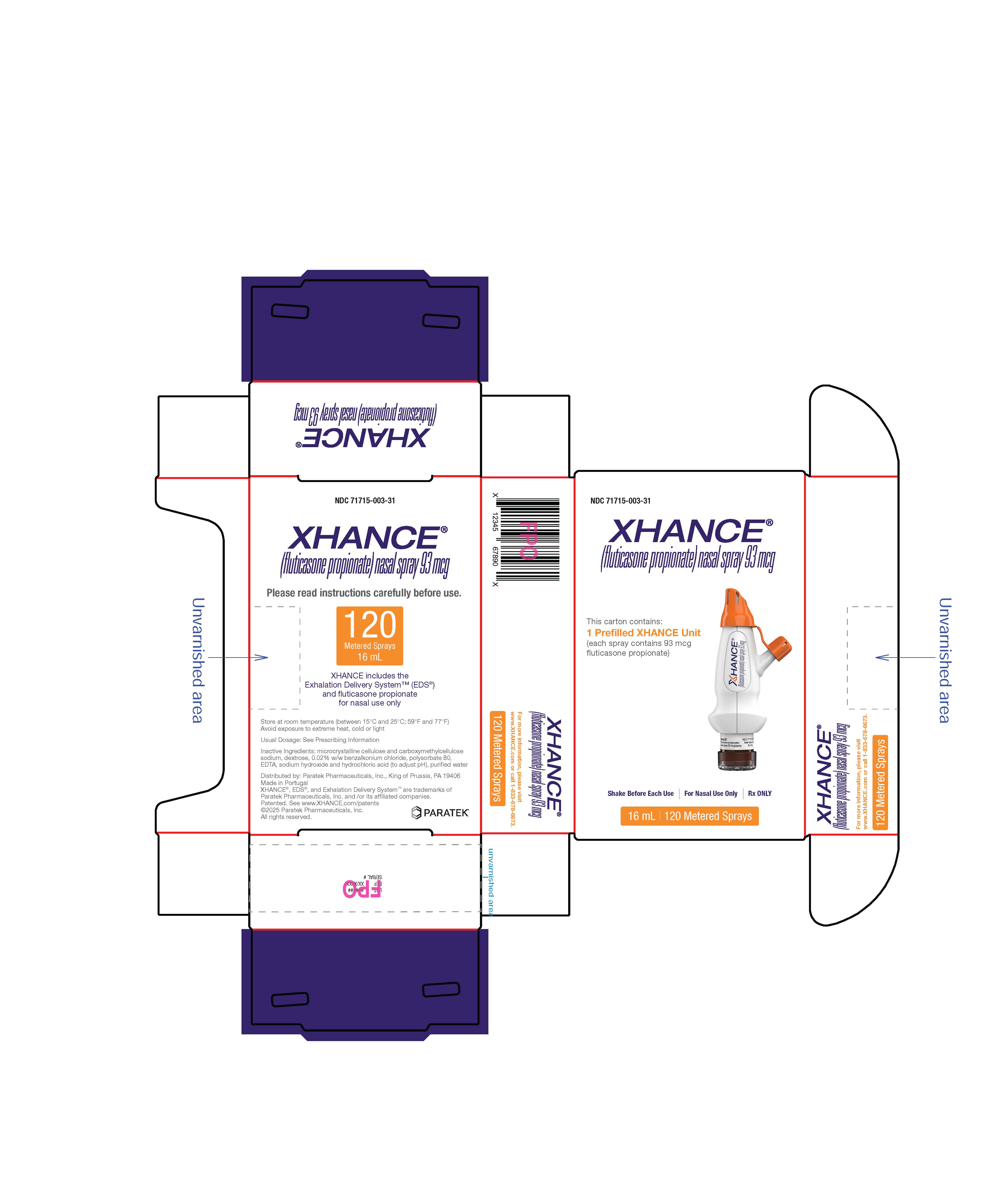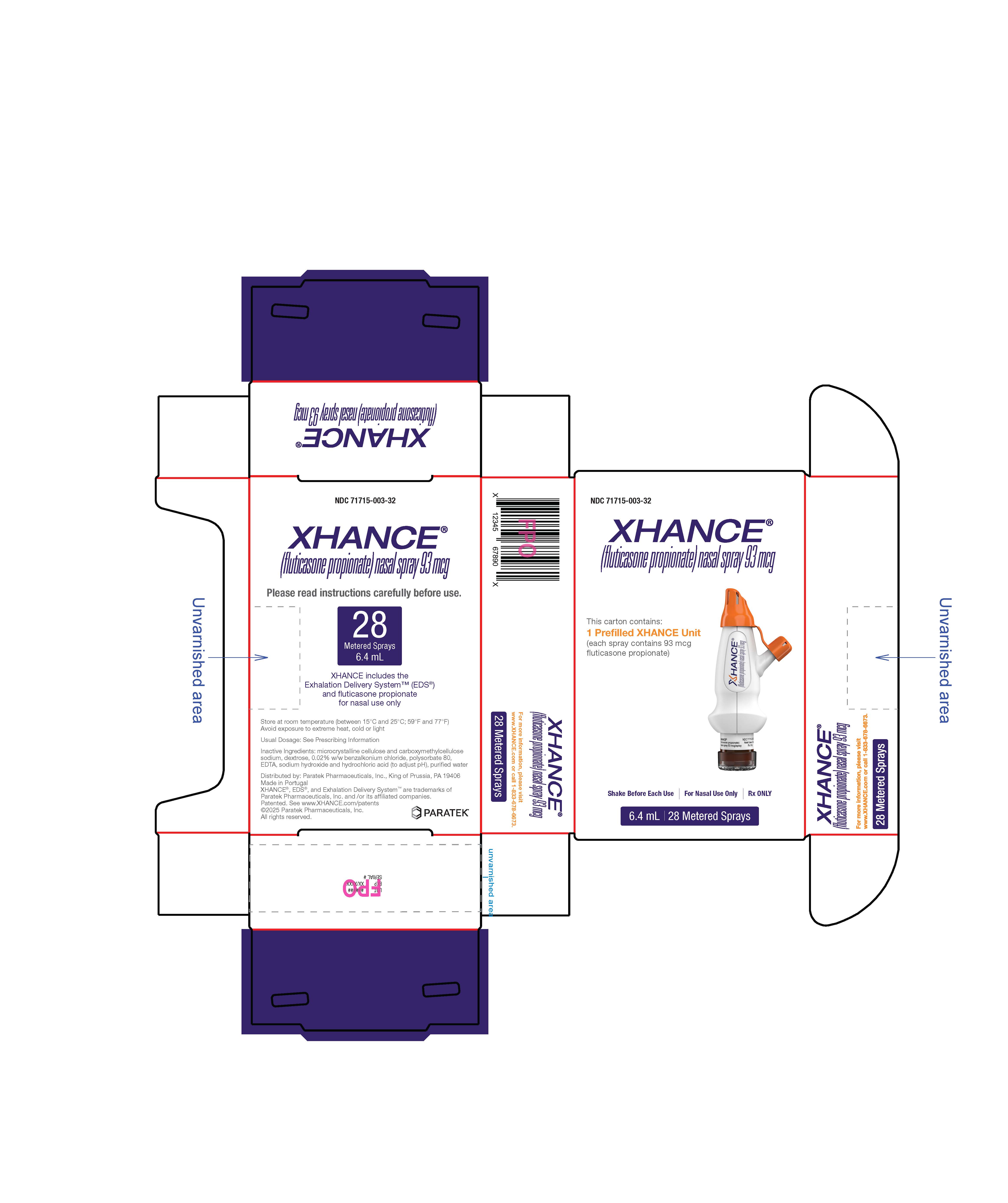 DRUG LABEL: XHANCE
NDC: 71715-003 | Form: SPRAY, METERED
Manufacturer: Paratek Pharmaceuticals, Inc.
Category: prescription | Type: HUMAN PRESCRIPTION DRUG LABEL
Date: 20260112

ACTIVE INGREDIENTS: FLUTICASONE PROPIONATE 93 ug/1 1
INACTIVE INGREDIENTS: MICROCRYSTALLINE CELLULOSE; CARBOXYMETHYLCELLULOSE SODIUM, UNSPECIFIED; DEXTROSE, UNSPECIFIED FORM; BENZALKONIUM CHLORIDE; POLYSORBATE 80; EDETATE DISODIUM; WATER; SODIUM HYDROXIDE; HYDROCHLORIC ACID

HIGHLIGHTS OF PRESCRIBING INFORMATION

These highlights do not include all the information needed to use XHANCE®safely and effectively. See full prescribing information for XHANCE®.
XHANCE® (fluticasone propionate) nasal spray
Initial U.S. Approval: 1994

RECENT MAJOR CHANGES

Indications and Usage (1.2) 03/2024

1 INDICATIONS AND USAGE

XHANCE is a corticosteroid indicated for the treatment of:

- Chronic rhinosinusitis with nasal polyps (CRSwNP) in adults. (1.1)
- Chronic rhinosinusitis without nasal polyps (CRSsNP) in adults. (1.2)

2 DOSAGE AND ADMINISTRATION

- Recommended Dosage: 186 mcg (1 spray per nostril) or 372 mcg (2 sprays per nostril) twice daily. (2.1)
- For nasal use only. Shake before use. Prime before initial use. (2.2)
- XHANCE is delivered into the nose by actuating the pump spray into one nostril while simultaneously blowing into the mouthpiece of the device. (2.2)

3 DOSAGE FORMS AND STRENGTHS

Nasal spray: 93 mcg of fluticasone propionate in each spray. (3)

4 CONTRAINDICATIONS

Hypersensitivity to any ingredient in XHANCE. (4)

5 WARNINGS AND PRECAUTIONS

- Local Nasal Adverse Reactions: epistaxis, erosion, ulceration, septal perforation, Candida albicansinfection, and impaired wound healing. Monitor patients periodically for signs of adverse effects on the nasal mucosa. Avoid use in patients with recent nasal ulcerations, nasal surgery, or nasal trauma. (5.1)
- Glaucoma and Cataracts may occur with long-term use. Consider referral to an ophthalmologist in patients who develop ocular symptoms or use XHANCE long-term. (5.2)
- Hypersensitivity reactions (e.g., anaphylaxis, angioedema, urticaria, contact dermatitis, rash, hypotension, and bronchospasm) have been reported after administration of fluticasone propionate. Discontinue XHANCE if such reactions occur. (5.3)
- Immunosuppression and Risk of Infection: potential increased susceptibility to or worsening of infections (e.g., existing tuberculosis; fungal, bacterial, viral, or parasitic infection; ocular herpes simplex). Use with caution in patients with these infections. More serious or even fatal course of chickenpox or measles can occur in susceptible patients. (5.4)
- Hypercorticism and adrenal suppression may occur with very high dosages or at the regular dosage in susceptible individuals. If such changes occur, discontinue XHANCE slowly. (5.5)
- Assess for decrease in bone mineral density initially and periodically thereafter. (5.7)

6 ADVERSE REACTIONS

- CRSwNP:The most common adverse reactions (incidence ≥ 3%) are epistaxis, nasal septal ulceration, nasopharyngitis, nasal mucosal erythema, nasal mucosal ulcerations, nasal congestion, acute sinusitis, nasal septal erythema, headache, and pharyngitis. (6.1)
- CRSsNP:The most common adverse reactions (incidence ≥ 3%) are epistaxis, headache, and nasopharyngitis (6.1).

To report SUSPECTED ADVERSE REACTIONS, contact Paratek Pharmaceuticals, Inc. at 1-833-678-6673 or FDA at 1-800-FDA-1088 or www.fda.gov/medwatch.

7 DRUG INTERACTIONS

Strong cytochrome P450 3A4 inhibitors (e.g., ritonavir, ketoconazole): Use not recommended. May increase risk of systemic corticosteroid effects. (7.1)

8 USE IN SPECIFIC POPULATIONS

Hepatic impairment: Monitor patients for signs of increased drug exposure. (8.6)

FULL PRESCRIBING INFORMATION

1 INDICATIONS AND USAGE

1.1 Chronic Rhinosinusitis with Nasal Polyps

XHANCE is indicated for the treatment of chronic rhinosinusitis with nasal polyps (CRSwNP) in adults.

1.2 Chronic Rhinosinusitis without Nasal Polyps

XHANCE is indicated for the treatment of chronic rhinosinusitis without nasal polyps (CRSsNP) in adults.

2 DOSAGE AND ADMINISTRATION

2.1 Recommended Dosage

The recommended dosage of XHANCE is 186 mcg (1 spray per nostril) or 372 mcg (2 sprays per nostril) twice daily (total daily dose of 372 mcg or 744 mcg). The maximum total daily dosage should not exceed 2 sprays in each nostril twice daily (total daily dose of 744 mcg).

Patients should use XHANCE at regular intervals since its effectiveness depends on regular use. Individual patients will experience a variable time to onset and different degrees of symptom relief.

The safety and efficacy of XHANCE when administered in excess of recommended doses have not been established.

2.2 Administration Information

- Shake XHANCE before each use.
- Administer XHANCE by the nasal route only. Avoid spraying directly on the nasal septum.

Priming

Before initial use, prime XHANCE by first gently shaking and then pressing the bottle 7 times or until a fine mist appears. Direct the spray into the air, away from the face. When XHANCE has not been used for ≥ 7 days, prime the pump again by shaking and releasing 2 sprays into the air, away from the face.

Administration Instructions

XHANCE is delivered into the nose by actuating the pump spray into one nostril while simultaneously blowing (exhaling) into the mouthpiece of the device. To administer XHANCE, insert the tapered tip of the cone-shaped nosepiece deep into one nostril and form a tight seal between the nosepiece and the nostril. Next, place the flexible mouthpiece into the mouth, bending it as necessary to maintain a tight seal with the nostril. Blow into the mouthpiece, and while continuing to blow, push the bottle up to actuate the spray pump. Continuing to blow through the mouth, but not inhaling or exhaling through the nose, at the time of actuation is important to achieve intended drug deposition. Repeat the process in the other nostril for a full dose [see Instructions for Use] .

3 DOSAGE FORMS AND STRENGTHS

Nasal spray: Each spray delivers 93 mcg of fluticasone propionate.

4 CONTRAINDICATIONS

XHANCE is contraindicated in patients with hypersensitivity to any of the ingredients [see Warnings and Precautions (5.3) and Description (11)] .

5 WARNINGS AND PRECAUTIONS

5.1 Local Nasal Adverse Reactions

Epistaxis, Nasal Erosions and Ulcerations

In placebo-controlled clinical trials of 16 weeks duration, epistaxis, nasal erosions, and nasal ulcerations were reported more frequently in patients treated with XHANCE than those who received placebo [see Adverse Reactions (6.1)] .

Nasal Septal Perforation

Nasal septal perforations have been reported in patients following the nasal application of XHANCE. In placebo-controlled clinical trials of 16 weeks duration, nasal septal perforation was reported in 1 (0.3%) patient treated with XHANCE compared with none treated with placebo. The patient had a prior history of nasal/sinus surgery. Three (0.3%) patients treated with XHANCE in uncontrolled, open-label trials of 3 to 12 months duration developed nasal septal perforations.

As with any long term topical treatment of the nasal cavity, patients using XHANCE over several months or longer should be examined periodically for possible changes in the nasal mucosa. If a septal perforation is noted, discontinue XHANCE. Avoid spraying XHANCE directly on the septum.

CandidaInfection

In clinical trials with XHANCE, localized infections with Candida albicanshave been observed. Eight (0.9%) patients in uncontrolled, open-label trials of 3 to 12 months duration developed Candida albicansinfections (nasal, pharyngeal, esophageal or intestinal). If such an infection develops, it may require treatment with appropriate local therapy and discontinuation of XHANCE. Patients using XHANCE should be examined periodically for evidence of Candidainfection in the nasal and oropharyngeal mucosa.

Impaired Wound Healing

Because of the inhibitory effect of corticosteroids on wound healing, patients who have experienced recent nasal ulcerations, nasal surgery, or nasal trauma should avoid using XHANCE until healing has occurred.

5.2 Glaucoma and Cataracts

Nasal and inhaled corticosteroids, including fluticasone propionate, may result in the development of glaucoma and/or cataracts. In placebo-controlled clinical trials of 16 weeks duration, cataracts were reported in 4 (1.2%) patients treated with XHANCE, compared with 3 (1.9%) patients treated with placebo. Among these patients, 2 patients treated with XHANCE reported subcapsular cataracts compared with none treated with placebo. Eleven patients (1.2%) in uncontrolled, open-label trials of 3 to 12 months duration developed new or worsening cataracts, of which none were subcapsular. Therefore, close monitoring is warranted in patients with a change in vision or with a history of increased intraocular pressure (IOP), glaucoma, and/or cataracts. Consider referral to an ophthalmologist in patients who develop ocular symptoms or use XHANCE long-term.

5.3 Hypersensitivity Reactions Including Anaphylaxis

Hypersensitivity reactions (e.g., anaphylaxis, angioedema, urticaria, contact dermatitis, rash, hypotension, and bronchospasm) have been reported after administration of fluticasone propionate. XHANCE is contraindicated in patients with known hypersensitivity to fluticasone propionate or any of the ingredients of XHANCE. Discontinue XHANCE if such reactions (e.g., anaphylaxis, angioedema, urticaria, contact dermatitis, rash, hypotension, and bronchospasm) occur [see Contraindications (4) and Adverse Reactions (6.1)] .

5.4 Immunosuppression and Risk of Infection

Persons who are using drugs that suppress the immune system, such as corticosteroids, including XHANCE, are more susceptible to infections than healthy individuals and may experience a worsening of existing infections. Chickenpox and measles, for example, can have a more serious or even fatal course in susceptible adults using corticosteroids. In such adults who have not had these diseases or been properly immunized, particular care should be taken to avoid exposure. How the dose, route, and duration of corticosteroid administration affect the risk of developing a disseminated infection is not known. The contribution of the underlying disease and/or prior corticosteroid treatment to the risk is also not known. If a patient is exposed to chickenpox, prophylaxis with varicella zoster immune globulin (VZIG) may be indicated. If a patient is exposed to measles, prophylaxis with pooled intramuscular immunoglobulin (IG) may be indicated. (See the respective Prescribing Information for VZIG and IG.) If chickenpox develops, treatment with antiviral agents may be considered.

Corticosteroids should be used with caution, if at all, in patients with active or quiescent tuberculosis infections of the respiratory tract; systemic fungal, bacterial, viral, or parasitic infections; or ocular herpes simplex [see Adverse Reactions (6.1)] .

5.5 Hypercorticism and Adrenal Suppression

Hypercorticism and adrenal suppression may occur when nasal corticosteroids, such as XHANCE, are used at higher than recommended dosages or in susceptible individuals at recommended dosages. Since fluticasone propionate is absorbed into the circulation and can be systemically active at higher doses, recommended dosages of XHANCE should not be exceeded to avoid hypothalamic-pituitary-adrenal (HPA) dysfunction. A relationship between plasma levels of fluticasone propionate and inhibitory effects on stimulated cortisol production has been shown after 4 weeks of pulmonary treatment with fluticasone propionate inhalation aerosol. Since individual sensitivity to effects on cortisol production exists, physicians should consider this information when prescribing XHANCE.

Patients treated with XHANCE should be observed carefully for any evidence of systemic corticosteroid effects such as hypercorticism and adrenal suppression (including adrenal crisis). If such effects occur, the dosage of XHANCE should be reduced slowly, consistent with accepted procedures for reducing systemic corticosteroids, and other treatments for management of nasal symptoms should be considered. Particular care should be taken in observing patients postoperatively or during periods of stress for evidence of inadequate adrenal response.

The replacement of a systemic corticosteroid with a topical corticosteroid can be accompanied by signs of adrenal insufficiency. In addition, some patients may experience symptoms of corticosteroid withdrawal (e.g., joint and/or muscular pain, lassitude, depression). After withdrawal from systemic corticosteroids, a number of months are required for recovery of HPA function. Patients previously treated for prolonged periods with systemic corticosteroids and transferred to topical corticosteroids should be carefully monitored for acute adrenal insufficiency in response to stress such as trauma, surgery, infection (particularly gastroenteritis), or other conditions associated with severe electrolyte loss. In patients who have asthma or other clinical conditions requiring long-term systemic corticosteroid treatment, rapid decreases in systemic corticosteroid dosages may cause a severe exacerbation of their symptoms [see Adverse Reactions (6.1) and Clinical Pharmacology (12.2)] .

5.6 Drug Interactions with Strong Cytochrome P450 3A4 Inhibitors

The use of strong cytochrome P450 3A4 (CYP3A4) inhibitors (e.g., ritonavir, atazanavir, clarithromycin, indinavir, itraconazole, nefazodone, nelfinavir, saquinavir, ketoconazole, telithromycin, conivaptan, lopinavir, voriconazole) with XHANCE is not recommended because increased systemic corticosteroid adverse effects may occur [see Drug Interactions (7.1) and Clinical Pharmacology (12.3)] .

5.7 Reduction in Bone Mineral Density

Decreases in bone mineral density (BMD) have been observed with long-term oral inhalation of products containing corticosteroids into the lungs. The clinical significance of small changes in BMD with regard to long-term consequences such as fracture is unknown. Patients with major risk factors for decreased bone mineral content, such as prolonged immobilization, family history of osteoporosis, postmenopausal status, tobacco use, advanced age, poor nutrition, or chronic use of drugs that can reduce bone mass (e.g., anticonvulsants, oral corticosteroids), should be monitored and treated with established standards of care.

A 2-year trial in 160 patients (females aged 18 to 40 years, males aged 18 to 50 years) with asthma receiving chlorofluorocarbon (CFC)-propelled fluticasone propionate inhalation aerosol 88 or 440 mcg twice daily demonstrated no statistically significant changes in BMD at any time point (24, 52, 76, and 104 weeks of double-blind treatment) as assessed by dual-energy x-ray absorptiometry at lumbar regions L1 through L4.

5.8 Effect on Growth

Nasal corticosteroids, including XHANCE, may cause a reduction in growth velocity when administered to pediatric patients. The safety and effectiveness of XHANCE has not been established in pediatric patients [see Use in Specific Populations (8.4)] .

6 ADVERSE REACTIONS

The following clinically significant adverse reactions are described elsewhere in the labeling:

- Local Nasal Adverse Reactions: [see Warnings and Precautions (5.1)]
- Glaucoma and Cataracts [see Warnings and Precautions (5.2)]
- Hypersensitivity Reactions including Anaphylaxis [see Contraindications (4) and Warnings and Precautions (5.3)]
- Immunosuppression and Risk of Infection [see Warnings and Precautions (5.4)]
- Hypercorticism and Adrenal Suppression [see Warnings and Precautions (5.5)]
- Reduction in Bone Mineral Density [see Warnings and Precautions (5.7)]
- Effect on Growth [see Warnings and Precautions (5.8)]

6.1 Clinical Trials Experience

Because clinical trials are conducted under widely varying conditions, adverse reaction rates observed in the clinical trials of a drug cannot be directly compared with rates in the clinical trials of another drug and may not reflect the rates observed in practice.

Chronic Rhinosinusitis with Nasal Polyps

The safety data described below are based on two placebo-controlled clinical trials evaluating doses of a fluticasone propionate nasal spray with an exhalation delivery system from 93 mcg twice daily to 372 mcg twice daily. Both trials were 16-weeks in duration with an additional 8-week open-label extension. The trials included a total of 643 adult patients with bilateral nasal polyps and associated moderate or severe nasal congestion of which 161 received 93 mcg twice daily, 160 received 186 mcg twice daily, 161 received 372 mcg twice daily and 161 received placebo. The overall pooled safety data included 296 (46.0%) Female, 347 (54.0%) Male, 584 (90.8%) White, 39 (6.1%) Black, 9 (1.4%) Asian, and 11 (1.7%) patients classified as Other. Of these patients, 45 (7%) were 65 years of age or older.

Table 1displays adverse reactions with an incidence of ≥ 3% in the XHANCE 186 mcg and 372 mcg twice daily patients, and more common than placebo.

Table 1. Summary of Adverse Reactions with XHANCE Reported in ≥ 3% of Patients with CRSwNP and More Common Than Placebo in Placebo-Controlled Studies
 |  | XHANCE
Adverse Reaction | Placebo (N = 161) n (%) | 186 mcg bid* (N = 160) n (%) | 372 mcg bid^ (N = 161) n (%)
Epistaxis^1 | 4 (2.5) | 19 (11.9) | 16 (9.9)
Nasopharyngitis | 8 (5.0) | 3 (1.9) | 12 (7.5)
Nasal septal ulceration^2 | 3 (1.9) | 11 (6.9) | 12 (7.5)
Nasal congestion | 6 (3.7) | 7 (4.4) | 9 (5.6)
Acute sinusitis | 6 (3.7) | 7 (4.4) | 8 (5.0)
Headache | 5 (3.1) | 8 (5.0) | 6 (3.7)
Pharyngitis | 2 (1.2) | 2 (1.3) | 5 (3.1)
Nasal mucosal ulceration^2 | 2 (1.3) | 6 (3.8) | 4 (2.5)
Nasal mucosal erythema | 6 (3.7) | 9 (5.6) | 8 (5.0)
Nasal septal erythema | 3 (1.9) | 6 (3.8) | 7 (4.3)
*186 mcg bid = 1 spray per nostril twice daily
^372 mcg bid = 2 sprays per nostril twice daily
^1Includes spontaneous adverse reaction reports
^2Include ulcerations and erosions

Other adverse reactions with XHANCE observed with an incidence < 3% but ≥ 1% and more common than placebo included: nasal dryness, sinusitis, oropharyngeal pain, toothache, intraocular pressure increase, dizziness, abdominal discomfort, and weight increase.

5.0% of patients treated with XHANCE 186 mcg twice daily and 1.2% of patients treated with 372 mcg twice daily discontinued from the clinical trials prior to the open-label extension because of adverse reactions compared to 4.3% of patients treated with placebo.

There were no clinically relevant differences in the incidence of adverse reactions based on gender. Clinical trials did not include sufficient numbers of non-Caucasian patients or patients aged 65 years and older to determine whether they respond differently from Caucasian or younger patients, respectively.

Chronic Rhinosinusitis without Nasal Polyps

The safety of XHANCE was based on a pooled safety population that reflect the exposure of XHANCE in 367 adults with chronic rhinosinusitis with (CRSwNP) or without nasal polyps (CRSsNP) exposed for 24 weeks duration. XHANCE was studied in two randomized, placebo-controlled, multicenter trials (Trial 3 and Trial 4). Patients received either XHANCE 186 mcg (1 spray per nostril) twice daily, XHANCE 372 mcg (2 sprays per nostril) twice daily, or placebo delivered with an exhalation delivery system. The pooled safety population had a mean age of 49 years [age range: 18 to 87], and were 55% male, 94% White, 96% non-Hispanic or Latino, 4% Black or African American, and 2% Asian.

In these trials, 1.6% of patients treated with XHANCE 186 mcg (1 spray per nostril) twice daily and 1.6% of patients treated with 372 mcg (2 sprays per nostril) twice daily discontinued treatment due to adverse reactions compared to 2.7% of patients treated with placebo.

The most common adverse reactions that occurred at a rate of ≥ 3% in patients treated with XHANCE and at a higher rate in at least one treatment group than placebo from the pooled safety population (Trials 3 and 4) are shown in Table 2.

Table 2. Summary of Adverse Reactions with XHANCE Reported in ≥ 3% of Patients and More Common Than Placebo from Pooled Safety Population (Trials 3 and 4)^1
 |  | XHANCE
Adverse Reaction | Placebo (N = 187) n (%) | 186 mcg bid* (N = 184) n (%) | 372 mcg bid^ (N = 183) n (%)
Epistaxis | 1 (0.5%) | 9 (4.9%) | 20 (10.9%)
Headache | 7 (3.7%) | 4 (2.2%) | 10 (5.5%)
Nasopharyngitis | 8 (4.3%) | 9 (4.9%) | 7 (3.8%)
*186 mcg bid = 1 spray per nostril twice daily
^372 mcg bid = 2 sprays per nostril twice daily
^1Patients in Trial 3 included adults with CRSsNP and Trial 4 included adults with CRSsNP and CRSwNP

6.2 Postmarketing Experience

The following adverse reactions have been identified during postapproval use of XHANCE. Because these reactions are reported voluntarily from a population of uncertain size, it is not always possible to reliably estimate their frequency or establish a causal relationship to drug exposure.

Eye disorders:central serous chorioretinopathy

Respiratory, thoracic, and mediastinal disorders:dysphonia, nasal discomfort, and nasal dryness

Skin and subcutaneous tissue disorders:pruritus, rash

7 DRUG INTERACTIONS

7.1 Inhibitors of Cytochrome P450 3A4

Fluticasone propionate is a substrate of CYP3A4. The use of strong CYP3A4 inhibitors (e.g., ritonavir, atazanavir, clarithromycin, indinavir, itraconazole, nefazodone, nelfinavir, saquinavir, ketoconazole, telithromycin, conivaptan, lopinavir, voriconazole) with XHANCE is not recommended because increased systemic corticosteroid adverse effects may occur.

Ritonavir

A drug interaction trial with fluticasone propionate aqueous nasal spray in healthy subjects has shown that ritonavir (a strong CYP3A4 inhibitor) can significantly increase plasma fluticasone propionate exposure, resulting in significantly reduced serum cortisol concentrations [see Clinical Pharmacology (12.3)] . During postmarketing use, there have been reports of clinically significant drug interactions in patients receiving fluticasone propionate products with ritonavir, resulting in systemic corticosteroid effects including Cushing’s syndrome and adrenal suppression.

Ketoconazole

Coadministration of orally inhaled fluticasone propionate (1000 mcg) and ketoconazole (200 mg once daily) resulted in a 1.9-fold increase in plasma fluticasone propionate exposure and a 45% decrease in plasma cortisol area under the curve (AUC), but had no effect on urinary excretion of cortisol.

8 USE IN SPECIFIC POPULATIONS

8.1 Pregnancy

Risk Summary

Available data from published literature on the use of inhaled or nasal fluticasone propionate in pregnant women have not reported a clear association with adverse developmental outcomes. In animals, teratogenicity characteristic of corticosteroids, decreased fetal body weight, and/or skeletal variations in rats, mice, and rabbits were observed with subcutaneously administered maternal toxic doses of fluticasone propionate less than the maximum recommended human daily inhaled dose (MRHDID) on a mcg/m^2basis. However, fluticasone propionate administered via inhalation to rats decreased fetal body weight, but did not induce teratogenicity at a maternal toxic dose less than the MRHDID on a mcg/m^2basis (see Data). Experience with oral corticosteroids suggests that rodents are more prone to teratogenic effects from corticosteroids than humans.

The estimated background risk of major birth defects and miscarriage for the indicated population is unknown. All pregnancies have a background risk of birth defect, loss, or other adverse outcomes. In the U.S. general population, the estimated risk of major birth defects and miscarriages in clinically recognized pregnancies is 2% to 4% and 15% to 20%, respectively.

Data

Animal Data

In embryofetal development studies with pregnant rats and mice dosed by the subcutaneous route throughout the period of organogenesis, fluticasone propionate was teratogenic in both species. Omphalocele, decreased body weight, and skeletal variations were observed in rat fetuses, in the presence of maternal toxicity, at a dose approximately equivalent to the MRHDID (on a mcg/m^2basis with a maternal subcutaneous dose of 100 mcg/kg/day). The rat no observed adverse effect level (NOAEL) was observed at approximately 0.4 times the MRHDID (on a mcg/m^2basis with a maternal subcutaneous dose of 30 mcg/kg/day). Cleft palate and fetal skeletal variations were observed in mouse fetuses at a dose approximately 0.3 times the MRHDID (on a mcg/m^2basis with a maternal subcutaneous dose of 45 mcg/kg/day). The mouse NOAEL was observed with a dose approximately 0.1 times the MRHDID (on a mcg/m^2basis with a maternal subcutaneous dose of 15 mcg/kg/day).

In an embryofetal development study with pregnant rats dosed by the inhalation route throughout the period of organogenesis, fluticasone propionate produced decreased fetal body weights and skeletal variations, in the presence of maternal toxicity, at a dose approximately 0.34 times the MRHDID (on a mcg/m^2basis with a maternal inhalation dose of 25.7 mcg/kg/day); however, there was no evidence of teratogenicity. The NOAEL was observed with a dose approximately 0.1 times the MRHDID (on a mcg/m^2basis with a maternal inhalation dose of 5.5 mcg/kg/day).

In an embryofetal development study in pregnant rabbits that were dosed by the subcutaneous route throughout organogenesis, fluticasone propionate produced reductions of fetal body weights, in the presence of maternal toxicity, at doses approximately 0.02 times the MRHDID and higher (on a mcg/m^2basis with a maternal subcutaneous dose of 0.57 mcg/kg/day). Teratogenicity was evident based upon a finding of cleft palate for 1 fetus at a dose approximately 0.1 times the MRHDID (on a mcg/m^2basis with a maternal subcutaneous dose of 4 mcg/kg/day). The NOAEL was observed in rabbit fetuses with a dose approximately 0.002 times the MRHDID (on a mcg/m^2basis with a maternal subcutaneous dose of 0.08 mcg/kg/day).

Fluticasone propionate crossed the placenta following subcutaneous administration to mice and rats and oral administration to rabbits.

In a pre- and post-natal development study in pregnant rats dosed from late gestation through delivery and lactation (Gestation Day 17 to Postpartum Day 22), fluticasone propionate was not associated with decreases in pup body weight, and had no effects on developmental landmarks, learning, memory, reflexes, or fertility at doses up to 0.7 times the MRHDID (on a mcg/m^2basis with maternal subcutaneous doses up to 50 mcg/kg/day).

8.2 Lactation

Risk Summary

There are no available data on the presence of fluticasone propionate in human milk, the effects on the breastfed child, or the effects on milk production. Fluticasone propionate is present in rat milk (see Data). Other corticosteroids have been detected in human milk. However, fluticasone propionate concentrations in plasma after orally inhaled therapeutic doses are low, and therefore, concentrations in human breast milk are likely to be correspondingly low [see Clinical Pharmacology (12.3)] . The developmental and health benefits of breastfeeding should be considered along with the mother’s clinical need for XHANCE and any potential adverse effects on the breastfed child from XHANCE or from the underlying maternal condition.

Data

Subcutaneous administration of tritiated fluticasone propionate at a dose in lactating rats approximately 0.1 times the MRHDID for adults (on a mcg/m^2basis) resulted in measurable levels in milk.

8.4 Pediatric Use

The safety and effectiveness of XHANCE in pediatric patients have not been established.

Effects on Growth

Controlled clinical trials have shown that nasal corticosteroids may cause a reduction in growth velocity when administered to pediatric patients. This effect was observed in the absence of laboratory evidence of HPA axis suppression, suggesting that growth velocity is a more sensitive indicator of systemic corticosteroid exposure in pediatric patients than some commonly used tests of HPA axis function. The long-term effects of this reduction in growth velocity associated with nasal corticosteroids, including the impact on final adult height, are unknown. The potential for “catch-up” growth following discontinuation of treatment with nasal corticosteroids has not been adequately studied. The growth of pediatric patients receiving nasal corticosteroids should be monitored routinely (e.g., via stadiometry). The potential growth effects of prolonged treatment should be weighed against the clinical benefits obtained and the risks associated with alternative therapies.

Controlled clinical trials have shown that corticosteroids orally inhaled into the lungs may cause a reduction in growth in pediatric patients. In these trials, the mean reduction in growth velocity was approximately 1 cm/year (range: 0.3 to 1.8 cm/year) and appeared to depend upon dose and duration of exposure. The effects on growth velocity of treatment with corticosteroids orally inhaled into the lungs for over 1 year, including the impact on final adult height, are unknown. The growth of children and adolescents receiving corticosteroids should be monitored routinely (e.g., via stadiometry) [see Warnings and Precautions (5.8)] .

8.5 Geriatric Use

Clinical trials of XHANCE for Chronic Rhinosinusitis with Nasal Polyps did not include sufficient numbers of patients aged 65 years and older to determine whether they responded differently than younger patients. Other reported clinical experience with fluticasone administered nasally or orally inhaled has not identified differences in responses between the elderly and younger patients, but greater sensitivity of some older individuals cannot be ruled out.

There were 82 patients 65 years of age and older in clinical trials for Chronic Rhinosinusitis without Nasal Polyps [see Clinical Studies (14)] . Of the total number of XHANCE-treated patients in these studies, 51 (14%) were 65 years of age and older. No overall differences in safety and effectiveness of XHANCE have been observed between patients 65 years of age and older and younger adult patients.

8.6 Hepatic Impairment

Formal pharmacokinetic trials using XHANCE have not been conducted in subjects with hepatic impairment. Since fluticasone propionate is predominantly cleared by hepatic metabolism, impairment of liver function may lead to accumulation of fluticasone propionate in plasma. Therefore, patients with hepatic disease should be closely monitored.

8.7 Renal Impairment

Formal pharmacokinetic trials using XHANCE have not been conducted in subjects with renal impairment.

10 OVERDOSAGE

Overdosage may result in signs/symptoms of hypercorticism [see Warnings and Precautions (5.5)] .

11 DESCRIPTION

The active component of XHANCE is fluticasone propionate, a corticosteroid, having the chemical name S-(fluoromethyl) 6α,9-difluoro-11β,17-dihydroxy-16α-methyl-3oxoandrosta-1,4-diene-17β-carbothioate, 17‑propionate and the following chemical structure:

Fluticasone propionate is a white powder with a molecular weight of 500.57, and the empirical formula is C25H31F3O5S. It is practically insoluble in water, freely soluble in dimethylformamide, sparingly soluble in acetone and dichloromethane, and slightly soluble in 96% ethanol.

XHANCE (fluticasone propionate) nasal spray, 93 mcg, for nasal administration, with an exhalation delivery system that delivers an aqueous suspension of microfine fluticasone propionate having a particle size distribution in the range of 0 to 5 microns for topical nasal administration by means of a metering, atomizing spray pump and exhaled breath. XHANCE also contains microcrystalline cellulose and carboxymethylcellulose sodium, dextrose, benzalkonium chloride, polysorbate 80, edetate disodium dihydrate, sodium hydroxide and hydrochloric acid (to adjust pH), and purified water, and has a pH between 5 and 7.

Before initial use, prime XHANCE by gently shaking and then pressing the amber glass bottle 7 times or until a fine mist appears. When XHANCE has not been used for ≥ 7 days, prime again by releasing 2 sprays into the air, away from the face [see Dosage and Administration (2.2) and Instructions for Use] .

After priming, each spray delivers 93 mcg of fluticasone propionate in an aqueous suspension through the cone-shaped nosepiece. The system also has a flexible mouthpiece. Within the device is a non‑removable amber glass bottle with a metering spray pump, an applicator, and a valve that prevents release of breath until the bottle is pressed. A base covers the bottom of the bottle, and a removable orange cap covers both the nosepiece and mouthpiece.

12 CLINICAL PHARMACOLOGY

12.1 Mechanism of Action

Fluticasone propionate is a synthetic trifluorinated corticosteroid with anti-inflammatory activity. Fluticasone propionate has been shown in vitro to exhibit a binding affinity for the human glucocorticoid receptor that is 18 times that of dexamethasone, almost twice that of beclomethasone-17-monopropionate (BMP), the active metabolite of beclomethasone dipropionate, and over 3 times that of budesonide. Data from the McKenzie vasoconstrictor assay in man are consistent with these results. The clinical significance of these findings is unknown.

The precise mechanism through which fluticasone propionate affects CRSsNP and CRSwNP and associated inflammatory symptoms is not known. Corticosteroids have been shown to have a wide range of effects on multiple cell types (e.g., mast cells, eosinophils, neutrophils, macrophages, lymphocytes) and mediators (e.g., histamine, eicosanoids, leukotrienes, cytokines) involved in inflammation. The anti-inflammatory action of corticosteroids contributes to their efficacy. In 7 trials in adults, fluticasone propionate nasal spray decreased nasal mucosal eosinophils in 66% of patients (35% for placebo) and basophils in 39% of patients (28% for placebo). In addition, studies suggest that carbon dioxide, which is present in the exhaled breath delivered into the nose through the device, may influence inflammatory mediator activity and neuropeptide activity, possibly through mechanisms of action that also include removal of nitric oxide, change in pH, or positive pressure. The direct relationship of these findings to long-term symptom relief is not known.

12.2 Pharmacodynamics

HPA Axis Effect

The potential systemic effects of XHANCE on the HPA axis have not been evaluated.

Serum cortisol concentrations, urinary excretion of cortisol, and urine 6-β- hydroxycortisol excretion collected over 24 hours in 24 healthy subjects following 8 oral inhalations of fluticasone propionate 44, 110, and 220 mcg decreased with increasing dose. However, in patients with asthma treated with 2 oral inhalations of fluticasone propionate 44, 110, and 220 mcg twice daily for at least 4 weeks, differences in serum cortisol AUC0-12h(n = 65) and 24-hour urinary excretion of cortisol (n = 47) compared with placebo were not related to dose and generally not significant.

The potential systemic effects of orally inhaled fluticasone propionate on the HPA axis were also studied in subjects with asthma [see Warnings and Precautions (5.5) and Adverse Reactions (6)] . Fluticasone propionate given by oral inhalation aerosol at dosages of 440 or 880 mcg twice daily was compared with placebo in oral corticosteroid‑dependent subjects with asthma (range of mean dose of prednisone at baseline: 13 to 14 mg/day) in a 16-week trial. Consistent with maintenance treatment with oral corticosteroids, abnormal plasma cortisol responses to short cosyntropin stimulation (peak plasma cortisol less than 18 mcg/dL) were present at baseline in the majority of subjects participating in this trial (69% of subjects later randomized to placebo and 72% to 78% of subjects later randomized to fluticasone propionate HFA). At week 16, 8 subjects (73%) on placebo compared with 14 (54%) and 13 (68%) subjects receiving fluticasone propionate HFA (440 and 880 mcg twice daily, respectively) had poststimulation cortisol levels of less than 18 mcg/dL.

Cardiac Electrophysiology

A study specifically designed to evaluate the effect of XHANCE on the QT interval has not been conducted.

12.3 Pharmacokinetics

The activity of XHANCE is due to the parent drug, fluticasone propionate. Due to the low bioavailability by the nasal route, the majority of the pharmacokinetic data were obtained via other routes of administration.

Absorption

The mean (SD) peak exposure (Cmax) and total exposure (AUC0-∞) following administration of a dose of 186 mcg of XHANCE during exhalation were 17.2 ± 7.40 pg/mL and 111.7 ± 49.75 pg·h/mL, respectively, and were 25.3 ± 10.34 pg/mL and 171.7 ± 85.55 pg·h/mL, respectively, following a dose of 372 mcg of XHANCE in healthy subjects. The Cmaxand AUC0-∞following a dose of 372 mcg of XHANCE in patients with mild to moderate asthma were 28.7±18.72 pg/mL and 222.6±84.60 pg·h/mL, respectively.

Distribution

Following intravenous administration, the initial disposition phase for fluticasone propionate was rapid and consistent with its high lipid solubility and tissue binding. The volume of distribution averaged 4.2 L/kg.

The percentage of fluticasone propionate bound to human plasma proteins averaged 99%. Fluticasone propionate is weakly and reversibly bound to erythrocytes and is not significantly bound to human transcortin.

Local exposure within the nasal cavity with XHANCE will differ when used without exhalation through the device.

Elimination

Following intravenous dosing, fluticasone propionate showed polyexponential kinetics and had a terminal elimination half-life of approximately 7.8 hours. The total blood clearance of fluticasone propionate is high (average: 1093 mL/min), with renal clearance accounting for less than 0.02% of the total.

Metabolism: The only circulating metabolite detected in man is the 17β-carboxylic acid derivative of fluticasone propionate, which is formed through the CYP3A4 pathway. This metabolite had less affinity (approximately 1/2000) than the parent drug for the glucocorticoid receptor of human lung cytosol in vitro and negligible pharmacological activity in animal studies. Other metabolites detected in vitro using cultured human hepatoma cells have not been detected in man.

Excretion: Less than 5% of a radiolabeled oral dose was excreted in the urine as metabolites, with the remainder excreted in the feces as parent drug and metabolites.

Specific Populations

XHANCE was not studied in any special populations, and no gender-specific pharmacokinetic data have been obtained.

Pediatric Patients: XHANCE was not studied in pediatric patients, and no pediatric-specific pharmacokinetic data have been obtained with the product.

Patients with Hepatic and Renal Impairment: Formal pharmacokinetic studies using XHANCE have not been conducted in patients with hepatic or renal impairment. However, since fluticasone propionate is predominantly cleared by hepatic metabolism, impairment of liver function may lead to accumulation of fluticasone propionate in plasma. Therefore, patients with hepatic disease should be closely monitored.

Racial or Ethnic Groups: No significant difference in clearance (CL/F) of fluticasone propionate in Caucasian, African-American, Asian, or Hispanic populations has been observed.

Drug Interaction Studies

Inhibitors of Cytochrome P450 3A4

Ritonavir: Fluticasone propionate is a substrate of CYP3A4. Coadministration of fluticasone propionate and the strong CYP3A4 inhibitor, ritonavir, is not recommended based upon a multiple-dose, crossover drug interaction trial in 18 healthy subjects. Fluticasone propionate aqueous nasal spray (200 mcg once daily) was coadministered for 7 days with ritonavir (100 mg twice daily). Plasma fluticasone propionate concentrations following fluticasone propionate aqueous nasal spray alone were undetectable (< 10 pg/mL) in most subjects, and when concentrations were detectable, peak levels (Cmax) averaged 11.9 pg/mL (range: 10.8 to 14.1 pg/mL) and AUC0-τaveraged 8.43 pg·h/mL (range: 4.2 to 18.8 pg·h/mL). Fluticasone propionate Cmaxand AUC0-τincreased to 318 pg/mL (range: 110 to 648 pg/mL) and 3102.6 pg·h/mL (range: 1207.1 to 5662.0 pg·h/mL), respectively, after coadministration of ritonavir with fluticasone propionate aqueous nasal spray. This significant increase in plasma fluticasone propionate exposure resulted in a significant decrease (86%) in serum cortisol AUC.

Ketoconazole: Coadministration of fluticasone propionate orally inhaled into the lungs (1000 mcg) and ketoconazole (200 mg once daily) resulted in a 1.9-fold increase in plasma fluticasone propionate exposure and a 45% decrease in plasma cortisol AUC, but had no effect on urinary excretion of cortisol.

Following orally-inhaled fluticasone propionate alone, AUC2-lastaveraged 1559 pg·h/mL (range: 555 to 2906 pg·h/mL) and AUC2-∞averaged 2269 pg·h/mL (range: 836 to 3707 pg·h/mL). Fluticasone propionate AUC2-lastand AUC2-∞increased to 2781 pg·h/mL (range: 2489 to 8486 pg·h/mL) and 4317 pg·h/mL (range: 3256 to 9408 pg·h/mL), respectively, after coadministration of ketoconazole with orally-inhaled fluticasone propionate. This increase in plasma fluticasone propionate concentration resulted in a decrease (45%) in serum cortisol AUC.

Erythromycin: In a multiple-dose drug interaction study, coadministration of orally inhaled fluticasone propionate (500 mcg twice daily) and erythromycin (333 mg 3 times daily) did not affect fluticasone propionate pharmacokinetics.

13 NONCLINICAL TOXICOLOGY

13.1 Carcinogenesis, Mutagenesis, Impairment of Fertility

Fluticasone propionate demonstrated no tumorigenic potential in mice at oral doses up to 1000 mcg/kg (approximately 7 times the MRHDID for adults on a mcg/m^2basis) for 78 weeks or in rats at inhalation doses up to 57 mcg/kg (approximately equivalent to the MRHDID for adults on a mcg/m^2basis) for 104 weeks.

Fluticasone propionate did not induce gene mutation in prokaryotic or eukaryotic cells in vitro. No significant clastogenic effect was seen in cultured human peripheral lymphocytes in vitro or in the in vivo mouse micronucleus test.

Fertility and reproductive performance were unaffected in male and female rats at subcutaneous doses up to 50 mcg/kg (approximately 0.7 times the MRHDID for adults on a mcg/m^2basis).

14 CLINICAL STUDIES

14.1 Chronic Rhinosinusitis with Nasal Polyps

The efficacy of XHANCE was evaluated in two randomized, double-blind, parallel‑group, multicenter, placebo-controlled, dose-ranging trials in adults 18 years and older with Chronic Rhinosinusitis with Nasal Polyps (CRSwNP) and associated moderate to severe nasal congestion (Trial 1 [NCT01622569], Trial 2 [NCT01624662]). The two trials included a total of 646 patients [348 (53.9%) males and 298 (46.1%) females] with a mean age of 45.5 years. Patients were randomized 1:1:1:1 to receive 93 mcg, 186 mcg, or 372 mcg twice daily or placebo for a period of 16 weeks. At baseline 35.7%, 79.0%, and 18.3% had polyps graded as mild, moderate, or severe, respectively. In addition, 90.6% of patients reported previous use of a topical steroid nasal spray for the treatment of CRSwNP and 53.6% reported previous sinus surgery or polypectomy.

The co-primary efficacy endpoints were 1) change from baseline to Week 4 in nasal congestion / obstruction averaged over the preceding 7 days of treatment and 2) change from baseline to Week 16 in bilateral polyp grade. Nasal congestion was rated by the patient on a 0 to 3 categorical severity scale (0 = none, 1 = mild, 2 = moderate, 3 = severe) at the time immediately prior to the next dose (instantaneous). Polyp grade was determined by the clinician using nasal endoscopy. Polyps on each side of the nose were graded on a categorical scale (0 = No polyps; 1 = Mild – polyps not reaching below the inferior border of the middle turbinate; 2 = Moderate – polyps reaching below the inferior border of the middle concha, but not the inferior border of the inferior turbinate; 3 = Severe – large polyps reaching below the lower inferior border of the inferior turbinate).

Efficacy was demonstrated for both XHANCE 186-mcg twice daily and XHANCE 372-mcg twice daily (Table 3).

Table 3: Effect of XHANCE nasal spray in two randomized, placebo-controlled trials in patients with CRSwNP.
 | Placebo | XHANCE 186-mcg bid | XHANCE 372-mcg bid | Diff. (95% CI) XHANCE 186-mcg bid vs placebo | Diff. (95% CI) XHANCE 372-mcg bid vs placebo
Trial 1 (N) | 82 | 80 | 79
Baseline nasal congestion | 2.31 | 2.24 | 2.29
LS mean change from baseline in nasal congestion at week 4 | -0.24 | -0.54 | -0.62 | -0.30 (-0.48, -0.11) | -0.38 (-0.57, -0.19)
Baseline total bilateral polyp grade | 3.8 | 3.9 | 3.7
LS mean change from baseline in total bilateral polyp grade at week 16 | -0.45 | -1.03 | -1.06 | -0.59 (-0.93, -0.24) | -0.62 (-0.96, -0.27)
Trial 2 (N) | 79 | 80 | 82
Baseline nasal congestion | 2.29 | 2.20 | 2.25
LS mean change from baseline in nasal congestion at week 4 | -0.24 | -0.68 | -0.62 | -0.45 (-0.64, -0.25) | -0.38 (-0.58, -0.18)
Baseline total bilateral polyp grade | 3.8 | 3.9 | 3.9
LS mean change from baseline in total bilateral polyp grade at week 16 | -0.61 | -1.22 | -1.41 | -0.60 (-0.89, -0.31) | -0.80 (-1.08, -0.51)
bid= twice daily

There were no clinically relevant differences in effectiveness of XHANCE across subgroups of patients defined by gender, age, or race.

Onset of action, evaluated by determining the starting period that the treatment effect of XHANCE on daily instantaneous AM congestion score started to achieve statistical significance in comparison to placebo and roughly maintained thereafter, was generally observed within 2 weeks for both XHANCE doses.

14.2 Chronic Rhinosinusitis without Nasal Polyps

The efficacy of XHANCE for Chronic Rhinosinusitis without Nasal Polyps (CRSsNP) was evaluated in two 24-week randomized, double-blind, parallel-group, multicenter, placebo-controlled trials in 555 adults 18 years and older (Trial 3 [NCT03960580] and Trial 4 [NCT03781804]). Trial 3 included 223 patients with CRSsNP and Trial 4 included 332 patients with either CRSsNP (N=124) or CRSwNP (N=208). While Trial 4 included CRSwNP patients, efficacy results from Trials 3 and 4 are presented for CRSsNP patients only.

In both trials, patients were randomized 1:1:1 to receive XHANCE 186 mcg twice daily, XHANCE 372 mcg twice daily, or placebo, all administered nasally for 24 weeks. All patients enrolled in Trial 3 and Trial 4 had at least 2 active nasal symptoms (congestion/obstruction, discharge, facial pain or pressure, reduction or loss of smell) with a minimum nasal congestion score ≥1.5 out of 3 and a baseline CT scan showing ≥25% opacification of both ethmoid and at least 1 maxillary sinus. Refer to Table 4for the demographic and baseline characteristics of all randomized CRSsNP patients in Trials 3 and 4.

Table 4: Demographics and Baseline Characteristics of Trials 3 & 4
 | Trial 3 (N=223) | Trial 4 (N=124)
Mean age (years) (SD) | 48 (13) | 50 (14)
Male, n (%) | 112 (50) | 64 (52)
Race, n (%)
White | 220 (99) | 114 (92)
Asian | 0 | 6 (5)
Black or African American | 2 (1) | 4 (3)
Other | 1 (<1) | 0
Number (%) of patients with a history of environmental allergies | 69 (31) | 58 (47)
Number (%) of patients using standard-delivery nasal steroids at study entry | 57 (26) | 64 (52)
Mean number (SD) of acute sinusitis exacerbations where subject received an antibiotic or oral steroids in last year | 1.1 (1.4) | 1.8 (1.6)
^1SD = standard deviation

In both trials, the coprimary efficacy endpoints were 1) change from baseline at Week 4 in the composite symptom score (CSS) as determined by patients using a daily diary and 2) change from baseline at Week 24 in percent opacified sinus volume. CSS was the sum of the individual nasal symptom scores for congestion/obstruction, facial pain/pressure, and nasal discharge, each rated by the patient on a 0 to 3 categorical severity scale (0 = none, 1 = mild, 2 = moderate, 3 = severe) in the morning immediately prior to the next dose. Sinus opacification was measured by CT scan and scored using a 3-dimensional computer-assisted volumetric assessment using software to quantify the average percent of opacified volume in the ethmoid and maxillary sinuses.

Efficacy was demonstrated for both coprimary endpoints (CSS and percent opacified sinus volume) for XHANCE 186 mcg twice daily and XHANCE 372 mcg twice daily. Refer to Table 5for coprimary endpoint results. Improvements demonstrated in CSS at Week 4 with either dose of XHANCE remained at Weeks 8 and 12.

Table 5: LS Mean Change in Composite Symptom Scores (CSS)aat Week 4 and Percent Opacified Sinus Volume at Week 24 in Patients with CRSsNP in Trials 3 and 4
 | Placebo | XHANCE 186-mcg BID | XHANCE 372-mcg BID | Diff. (95% CI) XHANCE 186-mcg BID vs placebo | Diff. (95% CI) XHANCE 372-mcg BID vs placebo
Trial 3 (N) | 75 | 72 | 73
Baseline Mean CSSa | 6.2 | 5.9 | 6.0
LS mean change from baseline in CSS at week 4 | -0.8 | -1.5 | -1.7 | -0.7 (-1.3, -0.2) | -0.9 (-1.5, -0.4)
Baseline Percent of Opacified Sinus Volume | 64.1 | 60.5 | 61.5
LS mean change from baseline in Percent Opacified Sinus Volume at week 24 | 0.4 | -7.0 | -5.5 | -7.5 (-12.1, -2.8) | -5.9 (-10.6, -1.3)
Trial 4 (N)b | 41 | 41 | 40
Baseline Mean CSS | 5.7 | 5.5 | 5.8
LS mean change from baseline in CSS at week 4 | -0.7 | -1.6 | -1.6 | -0.9 (-1.6, -0.2) | -0.9 (-1.6, -0.2)
Baseline Percent of Opacified Sinus Volume | 61.9 | 63.0 | 60.7
LS mean change from baseline in Percent Opacified Sinus Volume at week 24 | -5.3 | -5.7 | -8.4 | -0.5 (-6.8, 5.9) | -3.2 (-9.5, 3.2)
Results were based on all patients who received at least one dose of study drug and had baseline measurements for coprimary endpoints, and at least one post-baseline CSS on or before Week 4.
aCSS range was 0 – 9. Scores were averaged over 7 days before a visit.
bData presented for Trial 4 patients with CRSsNP only
LS= Least Square; BID= twice daily; CI = Confidence Interval

Secondary efficacy endpoints included change from baseline in individual symptoms of the CSS (nasal congestion, nasal pain/pressure, and nasal discharge) at Week 4. Refer to Table 6for individual symptom score results.

Table 6: LS Mean Change in Individual Symptom Scoresaat Week 4 in Patients with CRSsNP in Trials 3 and 4
 | Placebo |  | XHANCE 186-mcg BID |  | XHANCE 372-mcg BID |  | Diff. (95% CI) XHANCE 186-mcg BID vs placebo | Diff. (95% CI) XHANCE 372-mcg BID vs placebo
 | Mean Baseline | LS Mean Change | Mean Baseline | LS Mean Change | Mean Baseline | LS Mean Change | Diff. (95% CI) XHANCE 186-mcg BID vs placebo | Diff. (95% CI) XHANCE 372-mcg BID vs placebo
Trial 3 (N) | 75 |  | 72 |  | 73
Nasal Congestion/ Obstruction | 2.3 | -0.3 | 2.1 | -0.6 | 2.2 | -0.7 | -0.3 (-0.5, -0.1) | -0.4 (-0.7, -0.2)
Facial Pain/Pressure | 1.8 | -0.3 | 1.7 | -0.4 | 1.7 | -0.5 | -0.2 (-0.4, 0.1) | -0.2 (-0.5, -0.0)
Nasal Discharge | 2.1 | -0.3 | 2.1 | -0.5 | 2.0 | -0.6 | -0.2 (-0.4, -0.0) | -0.3 (-0.5, -0.1)
Trial 4 (N)b | 41 |  | 41 |  | 40
Nasal Congestion/ Obstruction | 2.2 | -0.3 | 2.1 | -0.6 | 2.2 | -0.6 | -0.3 (-0.6, -0.1) | -0.3 (-0.6, -0.0)
Facial Pain/Pressure | 1.7 | -0.2 | 1.6 | -0.4 | 1.7 | -0.4 | -0.2 (-0.5, 0.0) | -0.2 (-0.5, 0.0)
Nasal Discharge | 1.9 | -0.2 | 1.8 | -0.6 | 1.9 | -0.6 | -0.4 (-0.6, -0.1) | -0.4 (-0.6, -0.1)
Individual symptom scores were not prespecified to adjust for multiplicity.
aScore range was 0-3.
bData presented for Trial 4 patients with CRSsNP only
LS= Least Square; BID= twice daily; CI = Confidence Interval

Acute Exacerbations

Acute exacerbations of chronic rhinosinusitis (AECRS), defined as a worsening of symptoms that required escalation of treatment (e.g., antibiotics, oral steroids, acute care visits), was assessed in the CRSsNP patients from pooled data (Trials 3 and 4) through Week 24. The rate of AECRS was reduced by 53% among patients in each XHANCE treatment group versus placebo. This was derived from incidence rate ratios of 0.47 (95% CI: 0.21, 1.08) and 0.47 (95% CI: 0.20, 1.09) among patients using XHANCE 186 mcg and 372 mcg twice daily versus placebo, respectively; which were not statistically significant.

16 HOW SUPPLIED/STORAGE AND HANDLING

XHANCE (fluticasone propionate) nasal spray is supplied as a non-removable amber glass bottle fitted with a metered-dose manual spray pump unit inside the white XHANCE device with a nasal applicator, valve mechanism, asymmetrical cone-shaped nosepiece, flexible mouthpiece, base, and orange cap in a box of 1. Each metered spray delivers 93 mcg of fluticasone propionate in an aqueous suspension through the cone shaped nosepiece.

They are supplied as follows:
1 bottle net fill content of 16mL that, after priming, will provide 120 metered sprays (NDC 71715-003-31) with FDA approved Patient Labeling [see Instructions for Use]. The bottle should be discarded after 120 metered sprays even though the bottle is not empty. Beyond 120 metered sprays, the correct amount of medication in each metered spray cannot be assured.

1 bottle net fill content of 6.4mL that, after priming, will provide 28 metered sprays (NDC 71715-003-32) with FDA approved Patient Labeling [see Instructions for Use]. The bottle should be discarded after 28 metered sprays even though the bottle is not empty. Beyond 28 metered sprays, the correct amount of medication in each metered spray cannot be assured.

Store at room temperature (between 15°C and 25°C; 59°F and 77°F), excursions permitted from 15°C to 30°C (59°F to 86°F). Avoid exposure to extreme heat, cold or light. Shake XHANCE before each use.

17 PATIENT COUNSELING INFORMATION

Advise the patient to read the FDA-approved patient labeling (Patient Informationand Instructions for Use).

Local Nasal Adverse Reactions

Inform patients that treatment with XHANCE may lead to adverse reactions, which include epistaxis, nasal erosions, and nasal ulceration. Candidainfection may also occur with treatment with XHANCE. In addition, XHANCE has been associated with nasal septal perforation and impaired wound healing. Patients who have experienced recent nasal ulcerations, nasal surgery, or nasal trauma should not use XHANCE until healing has occurred [see Warnings and Precautions (5.1)] .

Glaucoma and Cataracts

Inform patients that glaucoma and cataracts are associated with long-term use of nasal and orally inhaled corticosteroids, including fluticasone propionate, and may increase the risk of some eye problems. Consider regular eye exams. Advise patients to notify their healthcare providers if a change in vision is noted while using XHANCE [see Warnings and Precautions (5.2)] .

Hypersensitivity Reactions, Including Anaphylaxis

Inform patients that hypersensitivity reactions, including anaphylaxis, angioedema, urticaria, contact dermatitis, rash, bronchospasm, and hypotension, may occur after administration of fluticasone. If such reactions occur during use with XHANCE, patients should discontinue use of the product [see Warnings and Precautions (5.3)] .

Immunosuppression and Risk of Infection

Warn patients who are on immunosuppressant doses of corticosteroids to avoid exposure to chickenpox or measles, and if they are exposed to consult their healthcare provider without delay. Inform patients of potential worsening of existing tuberculosis; fungal, bacterial, viral, or parasitic infections; or ocular herpes simplex [see Warnings and Precautions (5.4)] .

Hypercorticism and Adrenal Suppression

Advise patients that XHANCE may cause systemic corticosteroid effects of hypercorticism and adrenal suppression. Additionally, inform patients that deaths due to adrenal insufficiency have occurred during and after transfer from systemic corticosteroids. Patients should taper slowly from systemic corticosteroids if transferring to XHANCE [see Warnings and Precautions (5.5)] .

Reduction in Bone Mineral Density

Advise patients who are at an increased risk for decreased bone mineral density that the use of corticosteroids may pose an additional risk [see Warnings and Precautions (5.7)] .

Reduced Growth Velocity

The safety and effectiveness of XHANCE use in pediatric patients has not been established. Inform patients that corticosteroids administered by oral inhalation into the lungs or nasally may cause a reduction in growth velocity when administered to pediatric patients [see Warnings and Precautions (5.8)] .

Use Twice Daily for Best Effect

Inform patients that they should use XHANCE on a regular basis as directed. XHANCE, like other corticosteroids, does not have an immediate effect on CRSsNP or CRSwNP or symptoms. Individual patients will experience a variable time to onset and degree of symptom relief and the full benefit may not be achieved until treatment has been administered for up to 16 weeks or longer. Maximum benefit may not be reached for a period of months. Patients should not increase the prescribed dosage, but should contact their healthcare providers if symptoms do not improve or if the condition worsens.

If a patient missed a dose, the patient should be advised to take the dose as soon as they remember. The patient should not take more than the recommended dose for the day.

Keep Spray Out of Eyes and Mouth

Inform patients to avoid spraying XHANCE in their eyes and mouth.

How to Use XHANCE

It is important for patients to understand how to correctly administer XHANCE nasal spray using the exhalation delivery system. Advise the patient to carefully read the patient Instructions for Use. Any questions regarding use that the patient has should be directed to the physician or pharmacist.

Advise the patient to shake before each use.

The patient should note the difference in appearance of the cone-shaped, non-flexible nosepiece and the longer flexible mouthpiece.

The patient should be instructed to gently insert the tapered tip of the cone-shaped nosepiece deeply into the nose in order to gently expand the nasal passage and to create a tight seal between the nosepiece and the nostril. A seal must be maintained as the patient blows into the mouthpiece and actuates the spray pump.

To actuate the device, patients should be advised to push the bottle up while continuing to blow forcefully into the mouthpiece. Within the device is a valve that prevents the release of breath until the bottle is pushed. Pushing the bottle also actuates the spray pump, releasing a metered dose of aerosolized medication while simultaneously allowing a “burst” of exhaled breath to pass through the device. This helps deliver the medication deep into the patient’s nose.

Patients should be advised not to try to inhale (e.g., “sniff”) when blowing (exhaling) into the mouthpiece.

Patients should be advised not to block the other nostril because the exhaled breath must pass around the back of the nasal septum and out the other side of the nose.

Distributed by:

Paratek Pharmaceuticals, Inc.
King of Prussia, PA 19406

XHANCE®is a registered trademark of Paratek Pharmaceuticals, Inc. and/or its affiliated companies.
Patented. See www.xhance.com/patents

©2025 Paratek Pharmaceuticals, Inc. All rights reserved.

PATIENT INFORMATION

XHANCE® (ex hans)

(fluticasone propionate)

nasal spray, 93 mcg

What is XHANCE?

XHANCE is a prescription medicine used to treat:

- chronic rhinosinusitis with nasal polyps in adults.
- chronic rhinosinusitis without nasal polyps in adults.

It is not known if XHANCE is safe and effective in children.

Do not use XHANCEif you are allergic to fluticasone propionate or any of the ingredients in XHANCE. See the end of this Patient Information leaflet for a complete list of ingredients in XHANCE.

Before using XHANCE, tell your healthcare provider about all of your medical conditions, including if you:

- have or have had nasal sores, nasal surgery, or nasal injury.
- have eye problems, such as cataracts or glaucoma.
- have an immune system problem.
- have any type of viral, bacterial, or fungal infection.
- are exposed to chickenpox or measles.
- have weak bones (osteoporosis).
- have liver problems.
- are pregnant or plan to become pregnant. It is not known if XHANCE may harm your unborn baby.
- are breastfeeding or plan to breastfeed. It is not known if XHANCE passes into your breast milk and if it can harm your baby.

Tell your healthcare provider about all the medicines you take, including prescription and over-the-counter medicines, vitamins, and herbal supplements.

XHANCE and certain other medicines may interact with each other. This may cause serious side effects.

Especially tell your healthcare provider if you take antifungal or anti-HIV medicines.

Know the medicines you take. Keep a list of them to show your healthcare provider and pharmacist when you get a new medicine.

How should I use XHANCE?

Read the Instructions for Useleaflet for information about the right way to use XHANCE.

- Use XHANCE exactly as your healthcare provider tells you.
- Do notuse XHANCE more often than prescribed. Ask your healthcare provider if you have any questions.
- XHANCE is for use in your nose only. Do not spray it in your eyes or mouth.
- XHANCE may take several days of regular use for your symptoms to get better. It may take several months for the medicine to have its greatest effect. If your symptoms do not improve or get worse, call your healthcare provider.
- You will get the best results if you keep using XHANCE regularly twice each day without missing a dose. Do not stop using XHANCE unless your healthcare provider tells you to do so.
- If you miss a dose of XHANCE, take it as soon as you remember the same day. Do nottake more than your prescribed dose of XHANCE each day.

What are the possible side effects of XHANCE?

XHANCE may cause serious side effects, including:

- Nasal problems. Symptoms of nasal problems may include:
  - nose bleeds.
  - crusting in the nose.
  - sores (ulcers) in the nose.
  - hole in the cartilage of the nose (nasal septal perforation). A whistling sound when you breathe may be a symptom of nasal septum perforation.
  - thrush (candida), a fungal infection in your nose and throat. Tell your healthcare provider if you have any redness or white colored patches in your nose or mouth.
  - slow wound healing. You should not use XHANCE until your nose has healed if you have a sore in your nose, have had surgery on your nose, or if your nose has been injured.
- Eye problems including glaucoma and cataracts. You should have regular eye exams while you use XHANCE. Call your healthcare provider if you have vision changes while using XHANCE.
- Serious allergic reactions. Call your healthcare provider or get emergency medical care if you get any of the following signs of a serious allergic reaction:

- rash
- hives
- swelling of your face, mouth, and tongue

- breathing problems
- low blood pressure

- Weakened immune system and increased chance of getting infections (immunosuppression). Taking medicines that weaken your immune system makes you more likely to get infections and can make certain infections worse. These infections may include tuberculosis (TB), herpes simplex infections of the eyes (ocular herpes simplex infections), and infections caused by fungi, bacteria, viruses, and parasites. Avoid contact with people who have a contagious disease such as chickenpox or measles while using XHANCE. If you come in contact with someone who has chickenpox or measles, call your healthcare provider right away. Symptoms of an infection may include:

- fever
- pain
- aches
- chills

- feeling tired
- nausea
- vomiting

- Reduced adrenal function (adrenal insufficiency). Reduced adrenal function happens when your adrenal glands do not make enough steroid hormones. This can happen when you stop taking oral corticosteroid medicines (such as prednisone) and start taking medicine containing a steroid inhaled into the lungs or for use in the nose. Adrenal insufficiency can also happen when nasal corticosteroids, such as XHANCE, are used at a dose higher than the usual dose or in people who are likely to have adrenal insufficiency at the usual dose. This may be more likely to happen after surgery or during periods of stress. Symptoms of reduced adrenal function may include:

- tiredness
- weakness

- nausea and vomiting
- low blood pressure

- Weak bones (osteoporosis).
- Slowed growth in children. A child’s growth should be checked often.

The most common side effects of XHANCE in adults with chronic rhinosinusitis with nasal polyps include:

- nose bleeds
- sores (ulcers) in your nose
- pain or swelling of your nose or throat (nasopharyngitis)

- redness in your nose
- nasal congestion
- sinus infection
- headache

The most common side effects of XHANCE in adults with chronic rhinosinusitis without nasal polyps include:

- nose bleeds
- headache
- pain or swelling of your nose or throat (nasopharyngitis)

These are not all the possible side effects of XHANCE.

Call your doctor for medical advice about side effects. You may report side effects to FDA at 1-800-FDA-1088.

How should I store XHANCE?

- Store XHANCE at room temperature between 59°F and 77°F (15°C and 25°C).
- Protect XHANCE from extreme heat, cold and light.
- 1 bottle net fill content of 16mL that, after priming, will provide 120 metered sprays with FDA approved Patient Labeling [see Instructions for Use]. The bottle should be discarded after 120 metered sprays even though the bottle is not empty. Beyond 120 metered sprays, the correct amount of medication in each metered spray cannot be assured.
- 1 bottle net fill content of 6.4mL that, after priming, will provide 28 metered sprays with FDA approved Patient Labeling [see Instructions for Use]. The bottle should be discarded after 28 metered sprays even though the bottle is not empty. Beyond 28 metered sprays, the correct amount of medication in each metered spray cannot be assured.
- The XHANCE Bottle is made of glass. Do not remove the base from the bottle.

Keep XHANCE and all medicines out of the reach of children.

General information about the safe and effective use of XHANCE.

Medicines are sometimes prescribed for purposes other than those listed in a Patient Information leaflet. Do not use XHANCE for a condition for which it was not prescribed. Do not give your XHANCE to other people, even if they have the same symptoms that you have. It may harm them.

You can ask your pharmacist or healthcare provider for information about XHANCE that is written for health professionals.

What are the ingredients in XHANCE?

Active ingredient: fluticasone propionate

Inactive ingredients: microcrystalline cellulose, carboxymethylcellulose sodium, dextrose, benzalkonium chloride, polysorbate 80, edetate disodium dihydrate, sodium hydroxide and hydrochloric acid (to adjust pH), and purified water

Distributed by: Paratek Pharmaceuticals, Inc.

King of Prussia, PA 19406

XHANCE®is a registered trademark of Paratek Pharmaceuticals, Inc. and/or its affiliated companies.

Patented. See www.xhance.com/patents.

©2025 Paratek Pharmaceuticals, Inc. All rights reserved.

For more information, go to www.XHANCE.com or call 1-833-678-6673.

This Patient Information has been approved by the U.S. Food and Drug Administration

Revised: 11/2025

PRINCIPAL DISPLAY PANEL - Carton Label - Outside - 16 mL

NDC 71715-003-31

XHANCE®
(fluticasone propionate) nasal spray 93 mcg

This carton contains:
1 Prefilled XHANCE Unit
(each spray contains 93 mcg
fluticasone propionate)

Shake Before Each Use For Nasal Use Only Rx ONLY

16 mL 120 Metered Sprays

NDC 71715-003-31

XHANCE®
(fluticasone propionate) nasal spray 93 mcg

Please read instructions carefully before use.

XHANCE includes the
Exhalation Delivery System™ (EDS®)
and fluticasone propionate for nasal use only

Store at room temperature (between 15°C and 25°C; 59°F and 77°F)
Avoid exposure to extreme heat, cold or light

Usual Dosage: See Prescribing Information

Inactive Ingredients: microcrystalline cellulose and carboxymethylcellulose
sodium, dextrose, 0.02% w/w benzalkonium chloride, polysorbate 80,
EDTA, sodium hydroxide and hydrochloric acid (to adjust pH), purified water

Distributed by: Paratek Pharmaceuticals, Inc., King of Prussia, PA 19406
Made in Portugal
XHANCE®, EDS®, and Exhalation Delivery System™ are trademarks of
Paratek Pharmaceuticals, Inc. and /or its affliated companies.
Patented. See www.XHANCE.com/patents
©2025 Paratek Pharmaceuticals, Inc.
All rights reserved.

XHANCE®
(fluticasone propionate) nasal spray 93 mcg

For more information, please visit
www.XHANCE.com or call 1-833-678-6673.

PRINCIPAL DISPLAY PANEL - Carton Label - Outside - 6.4 mL

NDC 71715-003-32

XHANCE®
(fluticasone propionate) nasal spray 93 mcg

This carton contains:
1 Prefilled XHANCE Unit
(each spray contains 93 mcg
fluticasone propionate)

Shake Before Each Use For Nasal Use Only Rx ONLY

6.4mL 28 Metered Sprays

NDC 71715-003-32

XHANCE®
(fluticasone propionate) nasal spray 93 mcg

Please read instructions carefully before use.

XHANCE includes the
Exhalation Delivery System™ (EDS®)
and fluticasone propionate for nasal use only

Store at room temperature (between 15°C and 25°C; 59°F and 77°F)
Avoid exposure to extreme heat, cold or light

Usual Dosage: See Prescribing Information

Inactive Ingredients: microcrystalline cellulose and carboxymethylcellulose
sodium, dextrose, 0.02% w/w benzalkonium chloride, polysorbate 80,
EDTA, sodium hydroxide and hydrochloric acid (to adjust pH), purified water

Distributed by: Paratek Pharmaceuticals, Inc., King of Prussia, PA 19406
Made in Portugal
XHANCE®, EDS®, and Exhalation Delivery System™ are trademarks of
Paratek Pharmaceuticals, Inc. and /or its affliated companies.
Patented. See www.XHANCE.com/patents
©2025 Paratek Pharmaceuticals, Inc.
All rights reserved.

XHANCE®
(fluticasone propionate) nasal spray 93 mcg

For more information, please visit
www.XHANCE.com or call 1-833-678-6673.